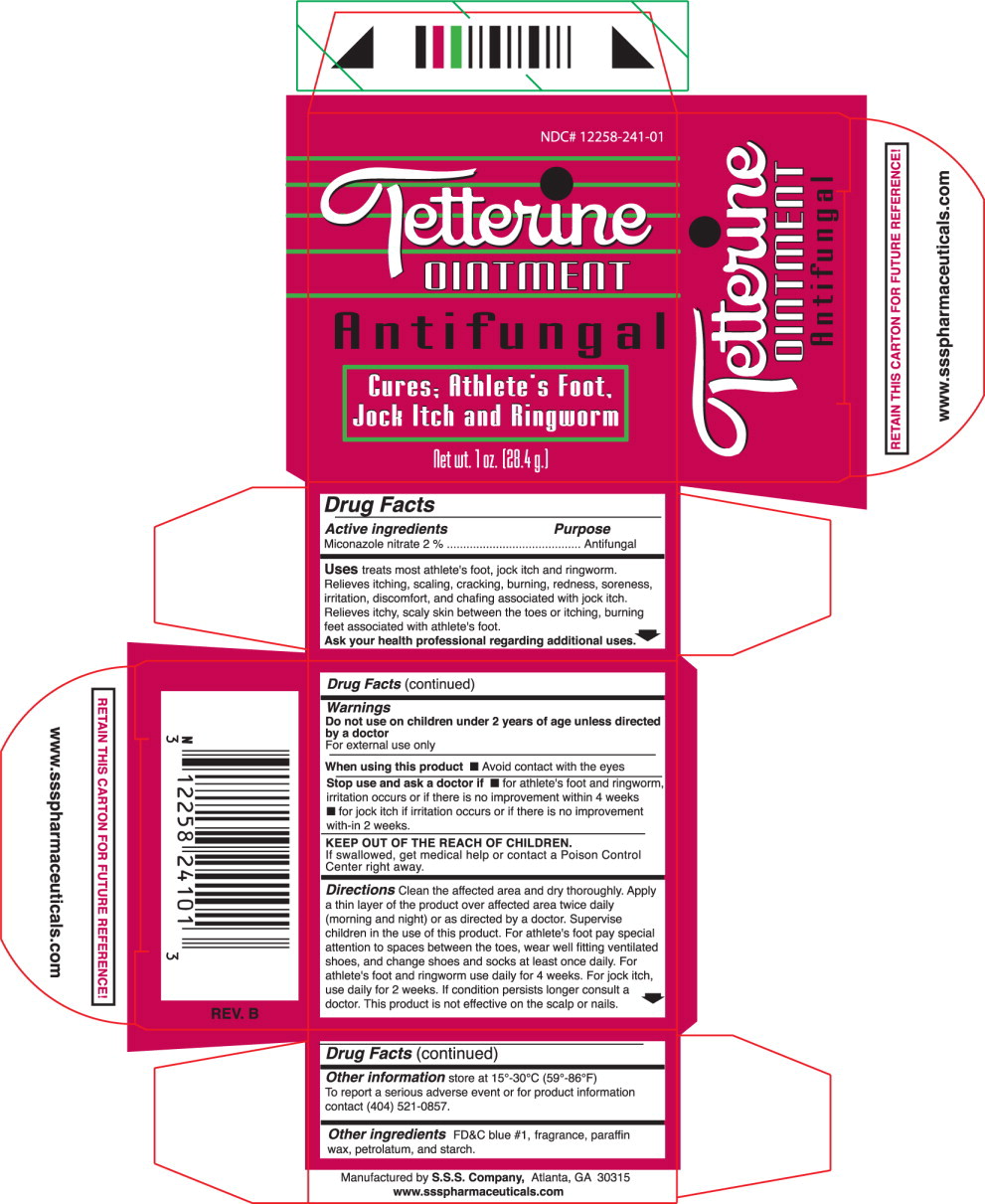 DRUG LABEL: Green Tetterine
NDC: 12258-241 | Form: OINTMENT
Manufacturer: S.S.S. Company
Category: otc | Type: HUMAN OTC DRUG LABEL
Date: 20260108

ACTIVE INGREDIENTS: MICONAZOLE NITRATE 2 g/100 g
INACTIVE INGREDIENTS: FD&C BLUE NO. 1; PARAFFIN; PETROLATUM; ALUMINUM STARCH OCTENYLSUCCINATE

DRUG FACTS

Active Ingredient:

Miconazole Nitrate 2%

Purpose:

Antifungal

Uses

treats most athlete's foot, jock itch and ringworm. Relieves itching, scaling, cracking, burning, redness, soreness, irritation, discomfort, and chafing associated with jock itch. Relieves itchy, scaly skin between the toes or itching, burning feet associated with athlete's foot.

Ask your health professional regarding additional uses

Warnings

Do not use on children under 2 years of age unless directed by a doctor

For external use only

When using this product

- Avoid contact with the eyes

Stop using and ask a doctor if

- for athlete's foot and ringworm, irritation occurs or if there is no improvement within 4 weeks.
- for jock itch if irritation occurs or if there is no improvement with-in 2 weeks

KEEP OUT OF REACH OF CHILDREN

If swallowed, get medical help or contact a Poison Control Center right away.

Directions

Clean the affected area and dry thoroughly. Apply a thin layer of the product over the affected area twice daily (morning and night) or as directed by a doctor. Supervise children in the use of this product. For athlete's foot pay special attention to spaces between the toes, wear well fitting ventilated shoes, and change shoes and socks at least once daily. For athlete's foot and ringworm use daily for 4 weeks. For jock itch, use daily for 2 weeks. If condition persists longer consult a doctor. This product is not effective on the scalp or nails.

Other Information

store at 15°-30°C (59°-86°F)

To report a serious adverse event or for product information contact (404) 521-0857.

Other Ingredients

FD&C blue #1, fragrance, paraffin wax, petrolatum, and starch

Principal Display Panel

NDC 12258-241-01

Tetterine®

Ointment

Antifungal

Cures: Athlete's Foot,

Jock Itch and Ringworm

Net wt. 1oz. (28.4g.)

Other Packaging Content

Manufactured by S.S.S. Company Atlanta, GA 1-800-237-3843

www.ssspharmaceuticals.com

Rev. B

RETAIN THIS CARTON FOR FUTURE REFERENCE!